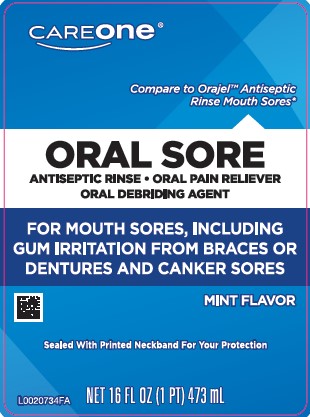 DRUG LABEL: Oral Sore Antiseptic
NDC: 72476-024 | Form: LIQUID
Manufacturer: Retail Business Services, LLC
Category: otc | Type: HUMAN OTC DRUG LABEL
Date: 20260206

ACTIVE INGREDIENTS: HYDROGEN PEROXIDE 15 mg/1 mL; MENTHOL 1 mg/1 mL
INACTIVE INGREDIENTS: ALCOHOL; FD&C BLUE NO. 1; EDETATE DISODIUM ANHYDROUS; METHYL SALICYLATE; PHOSPHORIC ACID; POLOXAMER 338; POLYSORBATE 20; SACCHARIN SODIUM; SORBITOL; WATER

Care One 024.000/024AA-AB
Oral Sore Antiseptic Rinse

Active ingredients

Hydrogen peroxide 1.5% (w/v)

Menthol 0.1% (w/v)

Purpose

Oral debriding agent/Oral antiseptic
Oral pain reliever

Uses

▪ first aid to help protect against bacterial contamination in minor oral wounds

▪ for temporary pain relief and ▪ temporary use in cleansing minor wounds or
minor gum inflammation resulting from: ▪ minor dental procedures ▪ dentures
▪ orthodontic appliances ▪ accidental injury ▪ other irritations of the mouth
and gums ▪ canker sores

▪ aids in the removal of: ▪ phlegm ▪ mucus ▪ other secretions associated with
occasional sore mouth

Warnings

for this product

Stop use and ask a doctor if

▪ sore throat is severe, persists for more than 2 days, is accompanied or followed by fever, headache, rash, nausea, or vomiting
▪ irritation, pain, or redness persists or worsens
▪ swelling, rash, or fever develops
▪ sore mouth symptoms do not improve in 7 days

When using this product

- do not swallow
- do not use more than 7 days unless directed by a dentist or doctor
- do not exceed recommended dosage

Keep out of reach of children

If more than used for rinsing is accidentally swallowed, get medical help or contact a Poison Control Center right away

Directions

Adults and children 2 years of age and older - swish two teaspoons (10 mL) around the mouth for at least 1 minute, then spit out; use up to 4 times daily or as directed by a dentist or physician

Children under 12 years of age - should be supervised in the use of the product

Children under 2 years of age - consult a dentist or doctor

Other information

- store at controlled room temperature 68-77°F (20-25°C)
- keep away from heat or direct sunlight

Inactive ingredients

alcohol (4.1% v/v), blue 1, disodium EDTA, methyl salicylate, phosphoric acid, poloxamer 338, polysorbate 20, sodium saccharin, sorbitol, water

ADVERSE REACTION

DISTRIBUTED BY ADUSA DISTRIBUTION, LLC

SALISBURY, NC 28147

For product questions or concerns,

contact us at 1-833-992-3872

Quality guaranteed or your money back.

*This product is not manufactured or distributed by Church & Dwight Co., Inc. distributor of Orajel Antiseptic Rinse Mouth Sores.

DSP-TN-21091 DSP-MO-20087

Principal display panel

CAREONE

Compare to Orajel Antispetic Rinse Mouth Sores*

ORAL SORE

ANTISEPTIC RINSE

ORAL PAIN RELIEVER

ORAL DEBRIDING AGENT

FOR MOUTH SORES, INCLUDING GUM IRRITATION FROM BRACES OR DENTURES AND CANKER SORES

MINT FLAVOR

Sealed With Printed Neckband For Your Protection

NET 16 FL OZ (1 PT) 473 mL